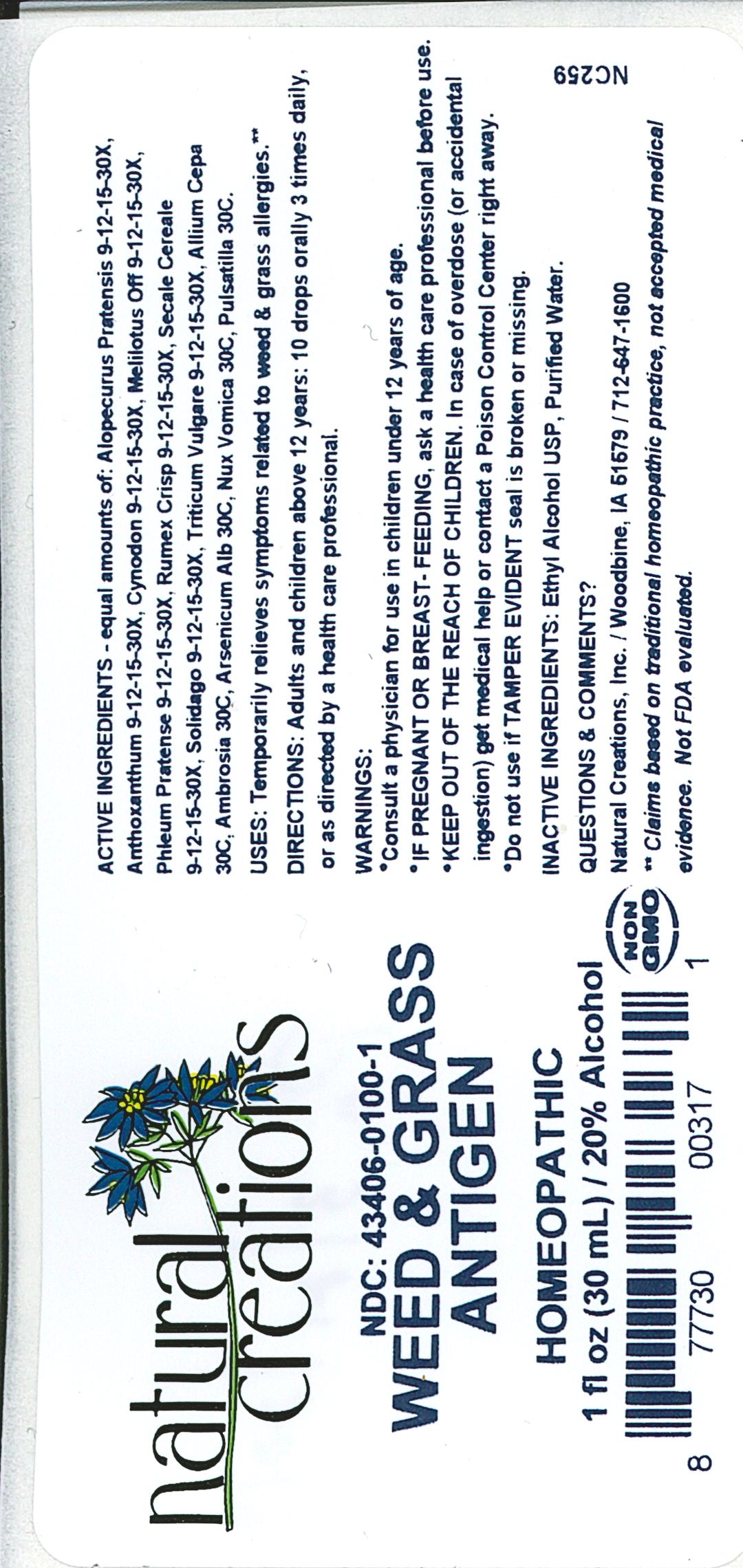 DRUG LABEL: Weed Grass Antigen
NDC: 43406-0100 | Form: LIQUID
Manufacturer: Natural Creations, Inc
Category: homeopathic | Type: HUMAN OTC DRUG LABEL
Date: 20181221

ACTIVE INGREDIENTS: ALOPECURUS PRATENSIS 30 [hp_X]/1 mL; ANTHOXANTHUM ODORATUM WHOLE 30 [hp_X]/1 mL; CYNODON DACTYLON WHOLE 30 [hp_X]/1 mL; MELILOTUS OFFICINALIS TOP 30 [hp_X]/1 mL; PHLEUM PRATENSE POLLEN 30 [hp_X]/1 mL; RUMEX CRISPUS ROOT 30 [hp_X]/1 mL; SECALE CEREALE WHOLE 30 [hp_X]/1 mL; SOLIDAGO VIRGAUREA FLOWERING TOP 30 [hp_X]/1 mL; WHEAT BRAN 30 [hp_X]/1 mL; ONION 30 [hp_C]/1 mL; AMBROSIA ARTEMISIIFOLIA WHOLE 30 [hp_C]/1 mL; ARSENIC TRIOXIDE 30 [hp_C]/1 mL; STRYCHNOS NUX-VOMICA SEED 30 [hp_C]/1 mL; PULSATILLA VULGARIS WHOLE 30 [hp_C]/1 mL
INACTIVE INGREDIENTS: ALCOHOL; WATER

Weed & Grass Antigen

ACTIVE INGREDIENT

ACTIVE INGREDIENTS - equal amounts of: Alopecurus Pratensis 9-12-15-30X, Anthoxanthum 9-12-15-30X, Cynodon 9-12-15-30X, Melilotus Off 9-12-15-30X, Phleum Pratense 9-12-15-30X, Rumex Crisp 9-12-15-30X, Secale Cereale 9-12-15-30X, Solidago 9-12-15-30X, Triticum Vulgare 9-12-15-30X, Allium Cepa 30C, Ambrosia 30C, Arsenicum Alb 30C, Nux Vomica 30C, Pulsatilla 30C

INDICATIONS AND USAGE

USES: Temporarily relives symptoms related to weed & grass allergies.**

PURPOSE

USES: Temporarily relives symptoms related to weed & grass allergies.**

DOSAGE AND ADMINISTRATION

DIRECTIONS: Adults & children above 12 years: 10 drops orally 3 times daily, or as directed by a health care professional.

KEEP OUT OF REACH OF CHILDREN

KEEP OUT OF THE REACH OF CHILDREN. In case of overdose (or accidental ingestion) get medical help or contact a Poison Control Center right away.

WARNINGS:

- Consult a physician for use in children under 12 years of age.
- IF PREGNANT OR BREAST-FEEDING, ask a health care professional before use.
- KEEP OUT OF THE REACH OF CHILDREN. In case of overdose (or accidental ingestion) get medical help or contact a Poison Control Center right away.
- A persistent cough may be a sign of a serious condition. If cough persists for more than 1 week, tends to recur, or is accompanied by fever, rash, or persistent headache, consult a doctor.
- Do not use if TAMPER EVIDENT seal is broken or missing.

INACTIVE INGREDIENTS: Ethyl Alcohol USP, Purified Water.

QUESTIONS & COMMENTS?

Natural Creations, Inc. / Woodbine, IA 51579 / 712-647-1600

REFERENCES

**Claims based on traditional homeopathic practice, not accepted medical evidence. Not FDA evaluated.

PACKAGE LABEL

NDC:43406-0100-1

Weed & Grass Antigen

HOMEOPATHIC

1 fl oz (30mL) / 20% Alcohol